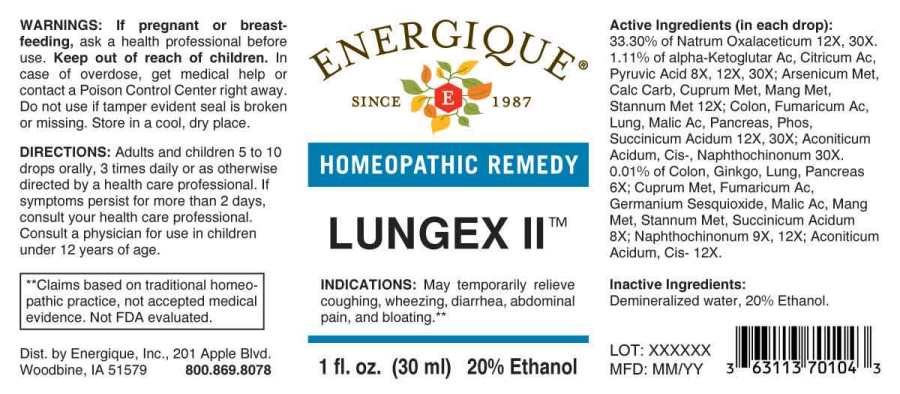 DRUG LABEL: Lungex
NDC: 44911-0439 | Form: LIQUID
Manufacturer: Energique, Inc.
Category: homeopathic | Type: HUMAN OTC DRUG LABEL
Date: 20241028

ACTIVE INGREDIENTS: GINKGO 6 [hp_X]/1 mL; SUS SCROFA COLON 6 [hp_X]/1 mL; SUS SCROFA LUNG 6 [hp_X]/1 mL; SUS SCROFA PANCREAS 6 [hp_X]/1 mL; GERMANIUM SESQUIOXIDE 8 [hp_X]/1 mL; COPPER 8 [hp_X]/1 mL; MANGANESE 8 [hp_X]/1 mL; TIN 8 [hp_X]/1 mL; OXOGLURIC ACID 8 [hp_X]/1 mL; CITRIC ACID MONOHYDRATE 8 [hp_X]/1 mL; FUMARIC ACID 8 [hp_X]/1 mL; MALIC ACID 8 [hp_X]/1 mL; PYRUVIC ACID 8 [hp_X]/1 mL; SUCCINIC ACID 8 [hp_X]/1 mL; 1,2-NAPHTHOQUINONE 9 [hp_X]/1 mL; ARSENIC 12 [hp_X]/1 mL; OYSTER SHELL CALCIUM CARBONATE, CRUDE 12 [hp_X]/1 mL; ACONITIC ACID 12 [hp_X]/1 mL; SODIUM DIETHYL OXALACETATE 12 [hp_X]/1 mL; PHOSPHORUS 12 [hp_X]/1 mL
INACTIVE INGREDIENTS: WATER; ALCOHOL

DRUG FACTS:

ACTIVE INGREDIENTS:

(in each drop): 33.30% Of Natrum Oxalaceticum 12X, 30X. 1.11% Of Alpha-Ketoglutaricum Acidum+ 8X, 12X, 30X; Citricum Acidum 8X, 12X, 30X, Pyruvic Acid 8X, 12X, 30X; Arsenicum Metallicum 12X, Calcarea Carbonica 12X, Cuprum Metallicum 12X, Manganum Metallicum 12X, Stannum Metallicum 12X; Colon (Suis) 12X, 30X, Fumaricum Acidum 12X, 30X, Lung (Suis) 12X, 30X, Malicum Acidum 12X, 30X, Pancreas Suis 12X, 30X, Phosphorus 12X, 30X, Succinicum Acidum 12X, 30X; Aconiticum Acidum, Cis- 30X, Naphthochinonum 30X, 0.01% Of Colon (Suis) 6X, Ginkgo Biloba 6X, Lung (Suis) 6X, Pancreas Suis 6X; Cuprum Metallicum 8X, Fumaricum Acidum 8X, Germanium Sesquioxide 8X, Malicum Acidum 8X, Manganum Metallicum 8X, Stannum Metallicum 8X, Succinicum Acidum 8X; Naphthochinonum 9X, 12X; Aconiticum Acidum, Cis- 12X.

INDICATIONS:

May temporarily relieve coughing, wheezing, diarrhea, abdominal pain, and bloating.**

**Claims based on traditional homeopathic practice, not accepted medical evidence. Not FDA evaluated.

WARNINGS:

If pregnant or breast-feeding, ask a health professional before use.

Keep out of reach of children. In case of overdose, get medical help or contact a Poison Control Center right away.

Do not use if tamper evident seal is broken or missing. Store in a cool, dry place.

Keep out of reach of children. In case of overdose, get medical help or contact a Poison Control Center right away.

DIRECTIONS:

Adults and children 5 to 10 drops orally, 3 times daily or as otherwise directed by a health care professional. If symptoms persist for more than 2 days, consult your health care professional. Consult a physician for use in children under 12 years of age.

INDICATIONS:

May temporarily relieve coughing, wheezing, diarrhea, abdominal pain, and bloating.**

**Claims based on traditional homeopathic practice, not accepted medical evidence. Not FDA evaluated.

INACTIVE INGREDIENTS:

Demineralized water, 20% Ethanol.

QUESTIONS:

Dist. by Energique, Inc.

201 Apple Blvd.

Woodbine, IA 51579 800-869-8078

PACKAGE LABEL DISPLAY:

ENERGIQUE

SINCE 1987

HOMEOPATHIC REMEDY

LUNGEX II

1 fl. oz. (30 ml)